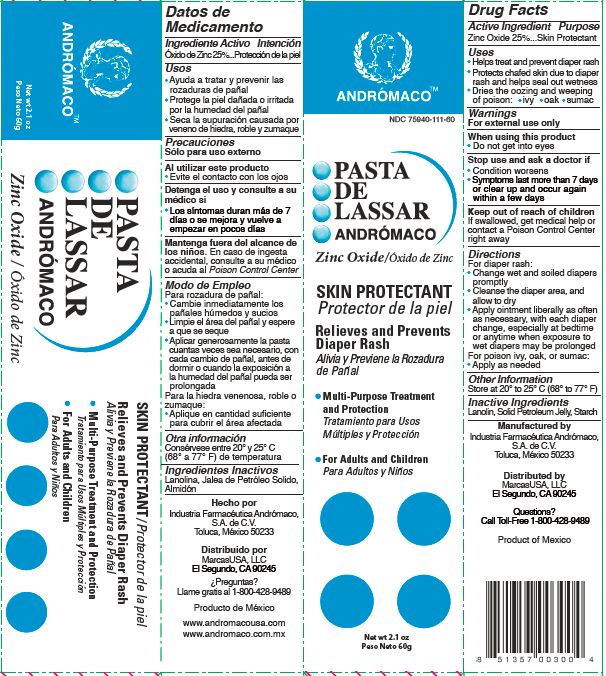 DRUG LABEL: Pasta de Lassar Andromaco
NDC: 75940-111 | Form: CREAM
Manufacturer: MarcasUSA LLC
Category: otc | Type: HUMAN OTC DRUG LABEL
Date: 20140701

ACTIVE INGREDIENTS: zinc oxide 250 mg/1 g
INACTIVE INGREDIENTS: LANOLIN; PETROLATUM; STARCH, CORN

Drug Facts

Active Ingredient Purpose

Zinc Oxide 25%........Skin Protectant

INDICATIONS AND USAGE

Uses

- Helps treat and prevent diaper rash
- Protects chafed skin due to diaper rash and helps seal out wetness
- Dries the oozing and weeping of poison:
  - ivy
  - oak
  - sumac

Warnings

For external use only

When using this product

- Do not get into eyes

Stop use and ask a doctor if

- Condition worsens
- Symptoms last more than 7 days or clear up and occur again within a few days

Keep out of reach of children

If swallowed, get medical help or contact a Poison Control Center right away

Directions

For diaper rash:

- Change wet and soiled diapers promptly
- Cleanse the diaper area, and allow to dry
- Apply ointment liberally as often as necessary, with each diaper change, especially at bedtime or anytime when exposure to wet diapers may be prolonged

For poison ivy, oak, or sumac:

- Apply as needed

Other Information

Store at 20° to 25°C (68° to 77°F)

Inactive Ingredients

Lanolin, Solid Petroleum Jelly, Starch

Manufactured by
Industria Farmacéutica Andrómaco
S.A. de C.V.
Toluca, México 50233

Distributed by
MarcasUSA, LLC
El Segundo, CA 90245

Questions?
Call Toll-Free 1-800-428-9489

Product of Mexico

Ingrediente Activo Intención

Oxido de Zinc 25%....Protección de la piel

Usos

- Ayuda a tratar y prevenir las rozaduras de pañal
- Protege la piel dañada o irritada por la humedad del pañal
- Seca la supuración causada por veneno de hiedra, roble y zumaque

Precauciones

Sólo para uso externo

Al utilizar este producto

- Evite el contacto con los ojos

Detenga el uso si la condición se empeora y consulte a su médico, si

- Los síntomas duran más de 7 días o se mejora y vuelve a empezar en pocos días

Mantenga fuera del alcance de los niños.

En caso de ingesta accidental, consulte a su médico o acuda al Poison Control Center

Modo de Empleo

Para rozadura de pañal:

- Cambie inmediatamente los pañales húmedos y sucios
- Limpie el área del pañal y espere a que se seque
- Aplicar generosamente la pasta cuantas veces sea necesario, con cada cambio de pañal, antes de dormir o cuando la exposición a la humedad del pañal pueda ser prolongada

Para la hiedra venenosa, roble o zumaque:

- Aplique en cantidad suficiente para cubrir el área afectada.

Otra información

Consérvese entre 20° y 25° C (68° a 77° F) de temperatura

Ingredientes Inactivos

Lanolina, Jalea de Petróleo Solido, Almidón

Hecho por
Industria Farmacéutica Andrómaco
S.A. de C.V.
Toluca, México 50233

Distribuido por
MarcasUSA, LLC
El Segundo, CA 90245

¿Preguntas?
Llame gratis al 1-800-428-9489

Producto de México

www.andromacousa.com
www.andromaco.com.mx

PRINCIPAL DISPLAY PANEL - 60 g Carton Label

ANDROMACO

NDC 75940-111-60

PASTA
DE
LASSAR
ANDRÓMACO

Zinc Oxide/Oxido de Zinc

SKIN PROTECTANT
Protector de la piel

Relieves and Prevents
Diaper Rash

Alivia y Previene la Rozadura
de Pañal

- Multi-Purpose Treatment
  and Protection
  Tratamiento para Usos
  Múltiples y Protección
- For Adults and Children
  Para Adultos y Niños

Net wt 2.1 oz
Peso Neto 60g